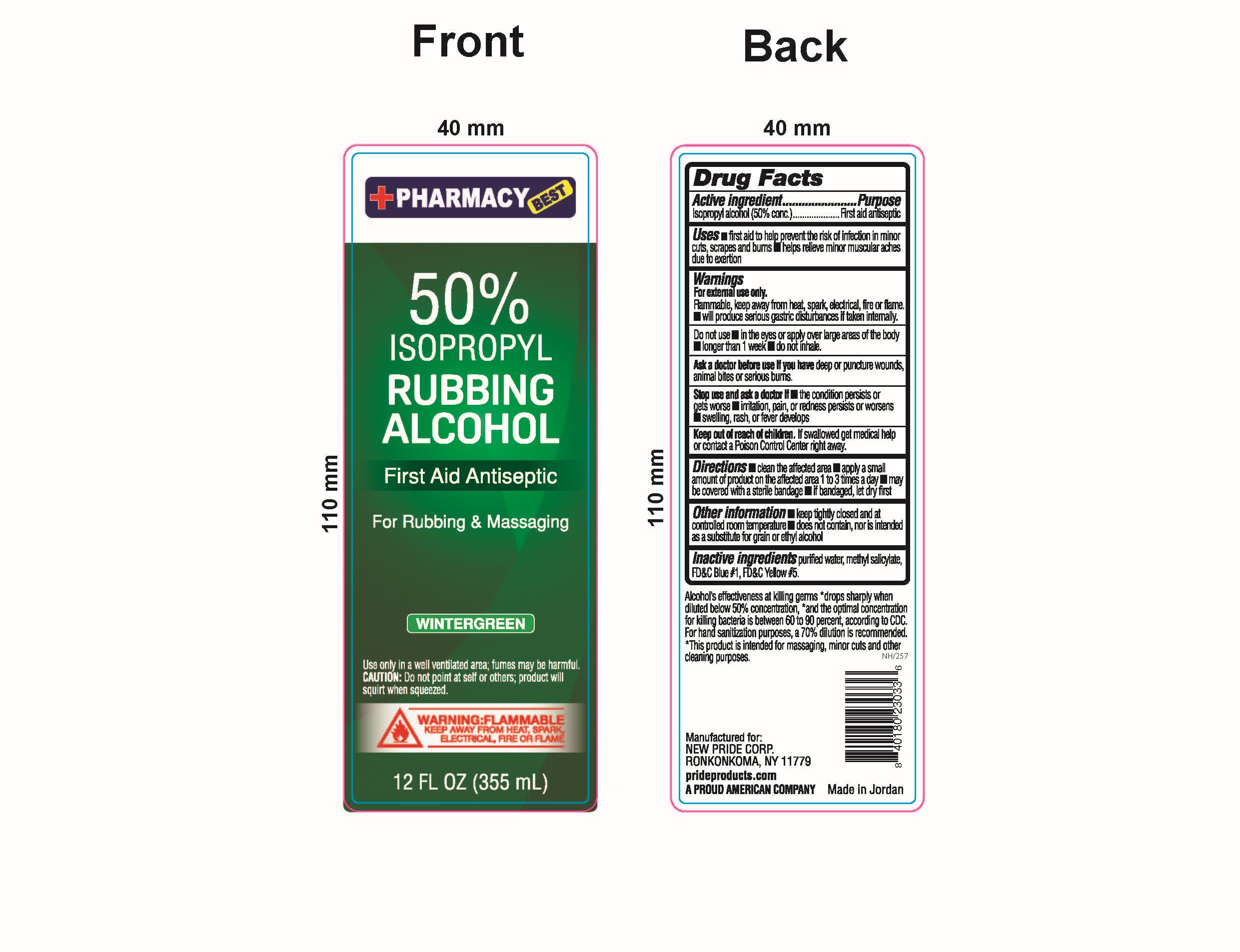 DRUG LABEL: 50% Rubbing Alcohol First Aid Antiseptic
NDC: 58037-702 | Form: LIQUID
Manufacturer: Pride Products Corp.
Category: otc | Type: HUMAN OTC DRUG LABEL
Date: 20240108

ACTIVE INGREDIENTS: ISOPROPYL ALCOHOL 50 mL/100 mL
INACTIVE INGREDIENTS: METHYL SALICYLATE; FD&C BLUE NO. 1; FD&C YELLOW NO. 5; WATER

Pride Products Corp. 50% Isopropyl Rubbing Alcohol First Aid Antiseptic (Wintergreen)

Drug Facts

ACTIVE INGREDIENT

Isopropyl alcohol (50% conc.)

PURPOSE

First aid antiseptic

USES

- first aid to help prevent the risk of infection in minor cuts, scrapes, and burns
- helps relieve minor muscular aches due to exertion

Warnings

For external use only.

Flammable, keep away from heat, spark, electrical, fire or flame.

- helps relieve minor muscular aches due to exertion.

Do not use

- in the eyes or apply over large areas of the body
- longer than 1 week
- do not inhale

Ask a doctor before use if you havedeep or puncture wounds, animal bites or serious burns.

Stop use and ask a doctor if

- the condition persists or gets worse
- irritation, pain, or redness persists or worsens
- swelling, rash, or fever develops

Keep out of reach of children.If swallowed get medical help or contact a Poison Control Center right away.

Directions

- clean the affected area
- apply a small amount of product on the affected area 1 to 3 times a day
- may be covered with a sterile bandage
- if bandaged, let dry first

Other information

- keep tightly closed at controlled room temperature
- does not contain, nor is intended as a substitute for grain or ethyl alcohol

INACTIVE INGREDIENT

Purified water, methyl salicylate, FD&C Blue #1, FD&C Yellow #5.

RECENT MAJOR CHANGES

Incorrect heading selected

PACKAGE LABEL

PACKAGE LABEL

50% ISOPROPYL RUBBING ALCOHOL

First Aid Antiseptic

For Rubbing & Massaging

WINTERGREEN

Use only in a well ventilated area; fumes may be harmful.

CAUTION: Do not point at self or others; product will squirt when squeezed.

WARNING: FLAMMABLE

KEEP AWAY FROM HEAT, SPARK, ELECTRICAL, FIRE OR FLAME

12 FL OZ (355 mL)

Alcohol's effectiveness at killing germs *drops sharply when diluted below 50% concentration, *and the optimal concentration for killing bacteria is between 60 to 90 percent, according to CDC. For hand sanitization purposes, a 70% dilution is recommended. *This product is intended for massaging, minor cuts and other cleaning purposes.

Manufactured for:

NEW PRIDE CORP.

RONKONKOMA, NY 11779

prideproducts.com

A PROUD AMERICAN COMPANY

Made in Jordan